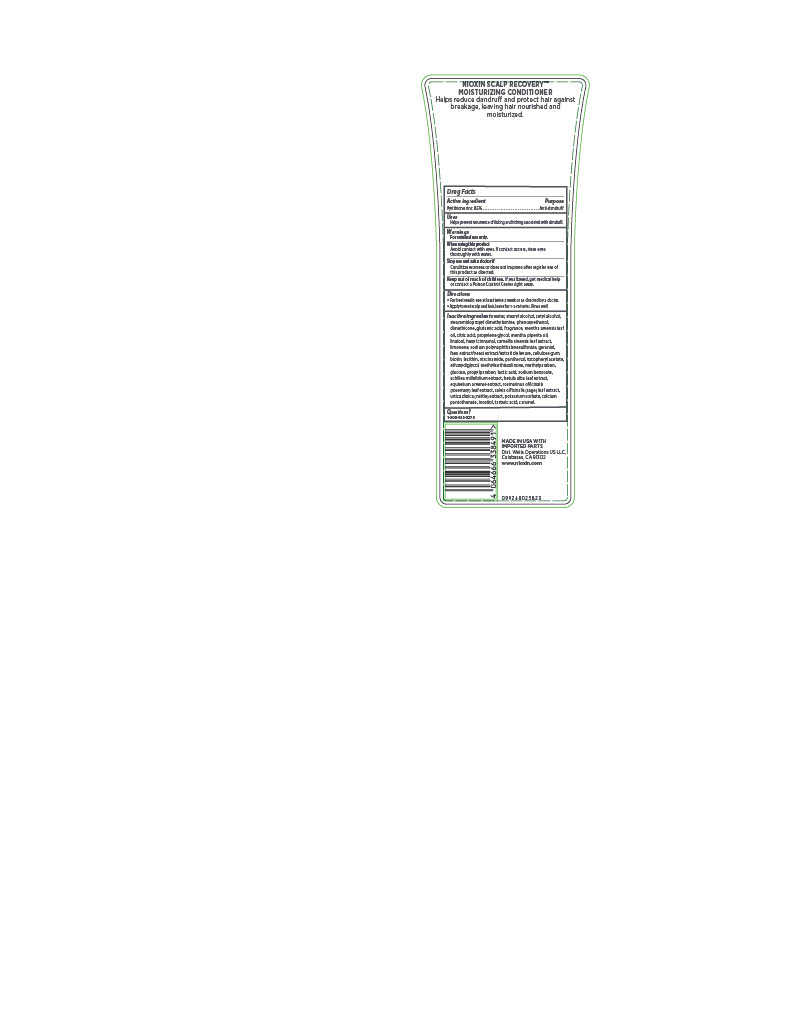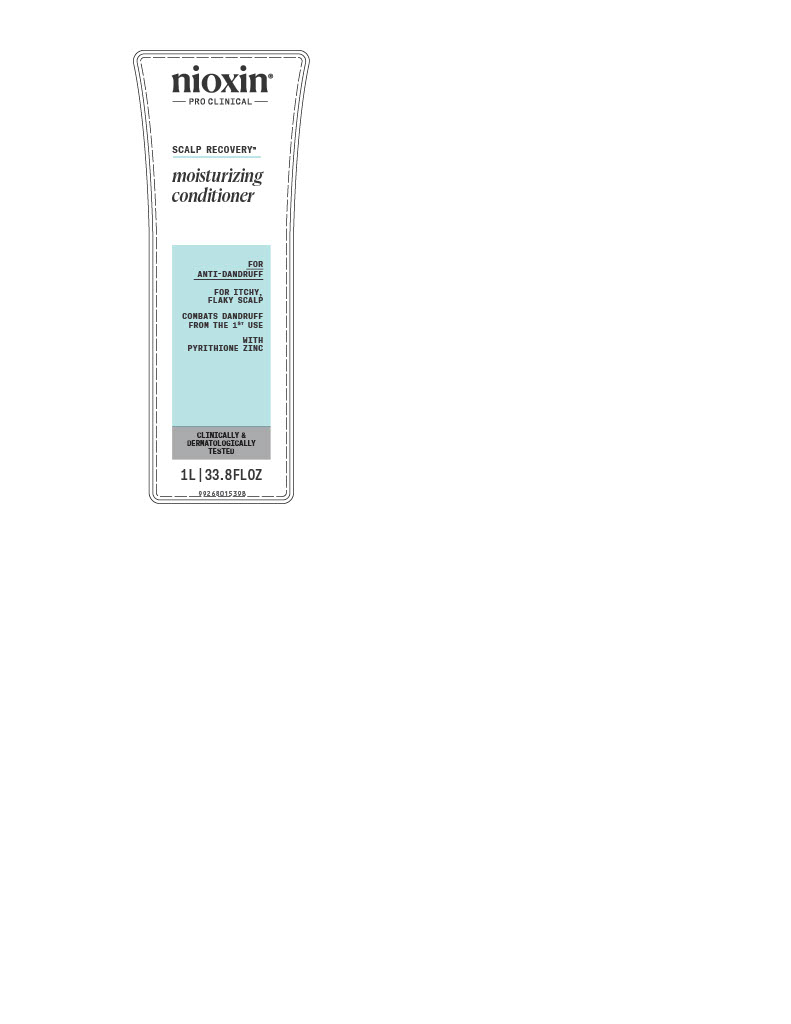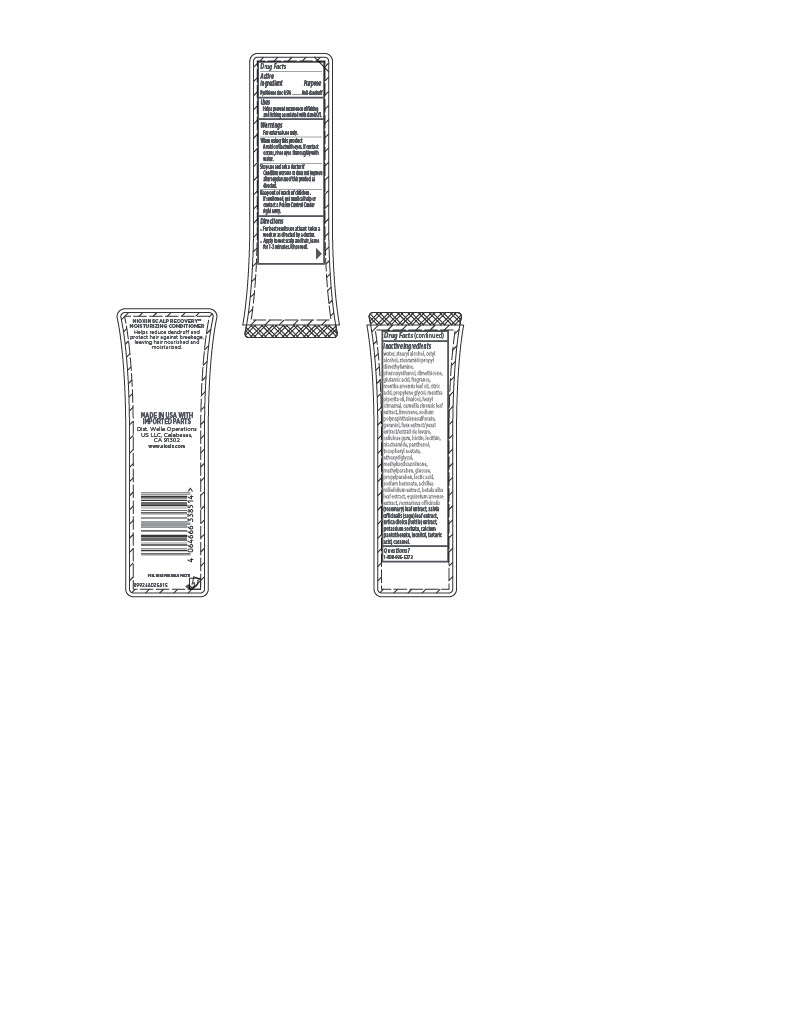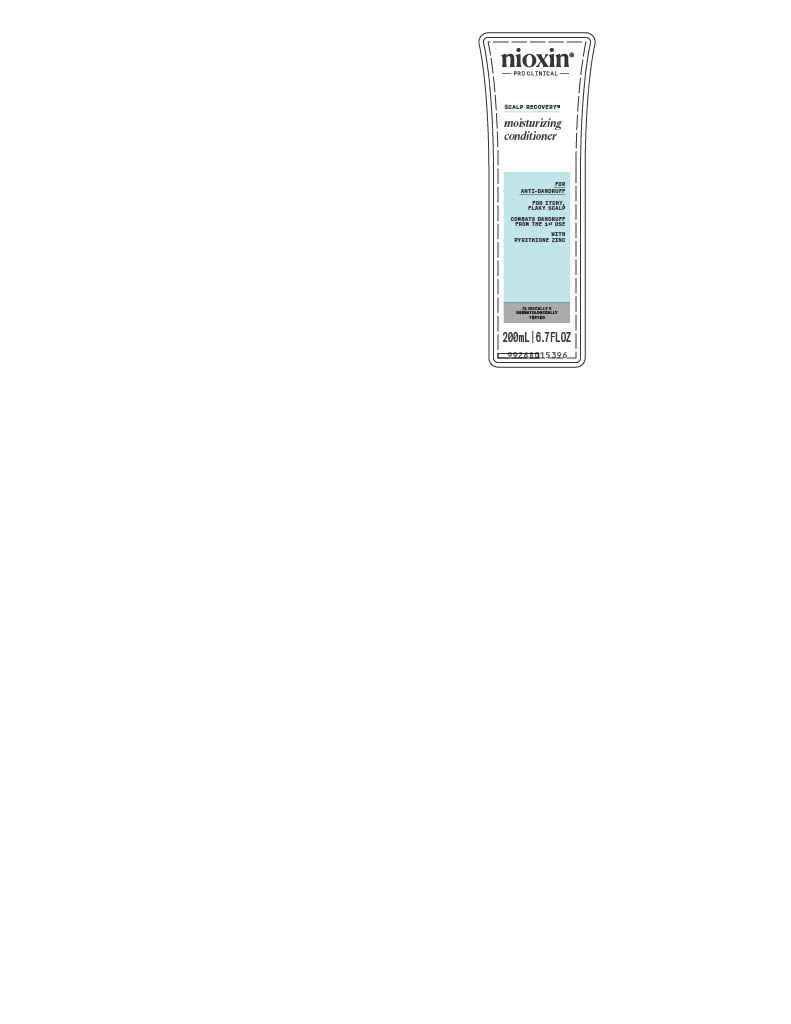 DRUG LABEL: nioxin PRO CLINICAL SCALP RECOVERY moisturizing conditioner
NDC: 82157-012 | Form: LOTION
Manufacturer: Wella Operations US LLC
Category: otc | Type: HUMAN OTC DRUG LABEL
Date: 20251125

ACTIVE INGREDIENTS: PYRITHIONE ZINC 0.5 g/100 mL
INACTIVE INGREDIENTS: DIMETHICONE; NIACINAMIDE; METHYLISOTHIAZOLINONE; BETULA ALBA LEAF; CALCIUM PANTOTHENATE; TARTARIC ACID; MENTHA ARVENSIS LEAF OIL; CITRIC ACID; HEXAMETHYLINDANOPYRAN; BIOTIN; URTICA DIOICA LEAF; INOSITOL; WATER; LECITHIN, SOYBEAN; PANTHENOL; ETHOXYDIGLYCOL; METHYLPARABEN; FORMALDEHYDE/SODIUM NAPHTHALENESULFONATE COPOLYMER (3000 MW); PROPYLPARABEN; LINALOOL, (+/-)-; HEXYL CINNAMAL; CAMELLIA SINENSIS LEAF; GERANIOL; GLUCOSE; LACTIC ACID; SAGE; CETYL ALCOHOL; STEARAMIDOPROPYL DIMETHYLAMINE; MENTHA PIPERITA (PEPPERMINT) OIL; PROPYLENE GLYCOL; STEARYL ALCOHOL; PHENOXYETHANOL; GLUTAMIC ACID; LIMONENE, (+/-)-; SODIUM BENZOATE; POTASSIUM SORBATE; CELLULOSE GUM; EQUISETUM ARVENSE BRANCH; .ALPHA.-TOCOPHEROL ACETATE, D-; ROSEMARY; CARAMEL; ACHILLEA MILLEFOLIUM; YEAST, UNSPECIFIED

nioxin PRO CLINICAL SCALP RECOVERY moisturizing conditioner

Drug Facts

Active Ingredient

Pyrithione zinc 0.5%

Purpose

Anti-dandruff

Uses

- Helps prevent recurrence of flaking and itching associated with dandruff.

Warnings

For external use only.

When using this product

- Avoid contact with eyes. If contact occurs, rinse eyes thoroughly with water.

Stop use and ask a doctor if

- Condition worsens or does not improve after regular use of this product as directed.

Keep out of reach of children.

- If swallowed, get medical help or contact a Poison Control Center right away.

Directions

- For best results use at least twice a week or as directed by a doctor.
- Apply to wet scalp and hair, leave for 1-3 minutes. Rinse well.

INACTIVE INGREDIENT

Inactive ingredients water, stearyl alcohol, cetyl alcohol, stearamidopropyl dimethylamine, phenoxyethanol, dimethicone, glutamic acid, fragrance, mentha arvensis leaf oil, citric acid, propylene glycol, mentha piperita oil, linalool, hexyl cinnamal, camellia sinensis leaf extract, limonene, sodium polynaphthalenesulfonate, geraniol, faex extract/yeast extract/extrait de levure, cellulose gum, biotin, lecithin, niacinamide, panthenol, tocopheryl acetate, ethoxydiglycol, methylisothiazolinone, methylparaben, glucose, propylparaben, lactic acid, sodium benzoate, achillea millefolium extract, betula alba leaf extract, equisetum arvense extract, rosmarinus officinalis (rosemary) leaf extract, salvia officinalis (sage) leaf extract, urtica dioica (nettle) extract, potassium sorbate, calcium pantothenate, inositol, tartaric acid, caramel.

Questions?

1-800-935-5273

NIOXIN SCALP RECOVERY™

MOISTURIZING CONDITIONER

Helps reduce dandruff and protect hair against breakage, leaving hair nourished and moisturized.

MADE IN USA WITH IMPORTED PARTS

Dist. Wella Operations US LLC, Calabasas, CA 91302

www.nioxin.com

PACKAGE LABEL

nioxin®

PRO CLINICAL

SCALP RECOVERY™

moisturizing conditioner

FOR ANTI-DANDRUFF

FOR ITCHY, FLAKY SCALP

COMBATS DANDRUFF FROM THE 1ST USE

WITH PYRITHIONE ZINC

CLINICALLY & DERMATOLOGICALLY TESTED

200 mL | 6.7 FL OZ

nioxin®

PRO CLINICAL

SCALP RECOVERY™

moisturizing conditioner

FOR ANTI-DANDRUFF

FOR ITCHY, FLAKY SCALP

COMBATS DANDRUFF FROM THE 1ST USE

WITH PYRITHIONE ZINC

CLINICALLY & DERMATOLOGICALLY TESTED

1L | 33.8 FL OZ